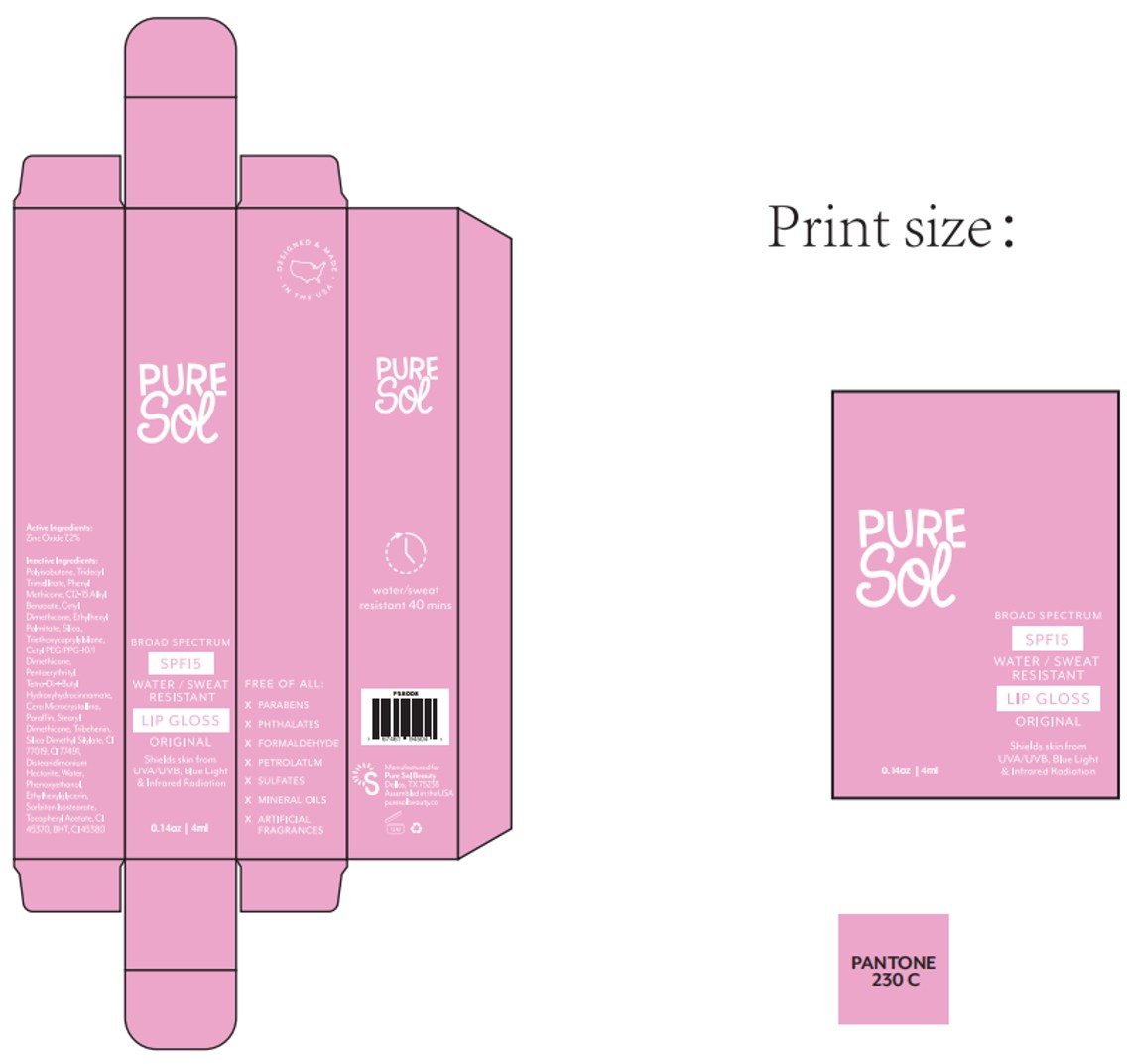 DRUG LABEL: PURE SOL  SPF15  Lip Gloss original
NDC: 84090-006 | Form: LIQUID
Manufacturer: Brand 2022b LLC
Category: otc | Type: HUMAN OTC DRUG LABEL
Date: 20251004

ACTIVE INGREDIENTS: ZINC OXIDE 7.2 g/100 mL
INACTIVE INGREDIENTS: TRIETHOXYCAPRYLYLSILANE; BHT; DISTEARDIMONIUM HECTORITE; STEARYL TRIMETHICONE; CI 75470; ETHYLHEXYLGLYCERIN; ALPHA-TOCOPHEROL ACETATE; SILICA; TRIDECYL TRIMELLITATE; CETYL PEG/PPG-10/1 DIMETHICONE (HLB 2); CI 45370; TRIBEHENIN; PHENOXYETHANOL; HYDROGENATED POLYISOBUTENE 8; PHENYL METHICONE (500 CST); WATER; CI 77891; SORBITAN ISOSTEARATE; CI 77491; FLAVOR SPICE MINT N&A110589; MICA; C12-15 ALKYL BENZOATE; ETHYLHEXYL PALMITATE; PENTAERYTHRITYL TETRA-DI-T-BUTYL HYDROXYHYDROCINNAMATE; MICROCRYSTALLINE WAX; CETYL DIMETHICONE/BIS-VINYLDIMETHICONE CROSSPOLYMER; SILICA DIMETHYL SILYLATE; PARAFFIN

84090-006-01. PURE SOL SPF15 Lip Gloss(Original)—liquid-4ml

ACTIVE INGREDIENT

Zinc Oxide 7.2%

PURPOSE

Helps prevent sunburn.

Keep out of reach of children.

If swallowed, get medical help or contact a Poison Control Center right away.

WARNINGS

For external use only

When using this product keep out of eyes.

Rinse with water to remove - do not use on broken skin.

INDICATIONS AND USAGE

Apply liberally and evenly 15 minutes before sun exposure.

■Reapply at least every two hours.

■Sun Protection Measures: Spending time in the sun increases

your risk of skin cancer and early skin aging. To decrease this risk,

regularly use a sunscreen with a Broad Spectrum SPF value of 15

DOSAGE AND ADMINISTRATION

Apply liberally and evenly 15 minutes before sun exposure.

■Reapply at least every two hours.

INACTIVE INGREDIENT

POLYISOBUTENE
TRIDECYL TRIMELLITATE
PHENYL METHICONE
C12-15 ALKYL BENZOATE
CETYL DIMETHICONE
ETHYLHEXYL PALMITATE
SILICA
TRIETHOXYCAPRYLYLSILANE
CETYL PEG/PPG-10/1 DIMETHICONE
PENTAERYTHRITYL TETRA-DI-t-BUTYL HYDROXYHYDROCINNAMATE
CERA MICROCRISTALLINA
PARAFFIN
STEARYL DIMETHICONE
TRIBEHENIN
CERA MICROCRISTALLINA
FLAVOR
SILICA DIMETHYL SILYLATE
CI 77019
CI 77491
DISTEARDIMONIUM HECTORITE
WATER
PHENOXYETHANOL
ETHYLHEXYLGLYCERIN
SORBITAN ISOSTEARATE
TOCOPHERYL ACETATE
CI 77891
CI 75470
BHT
CI 45370